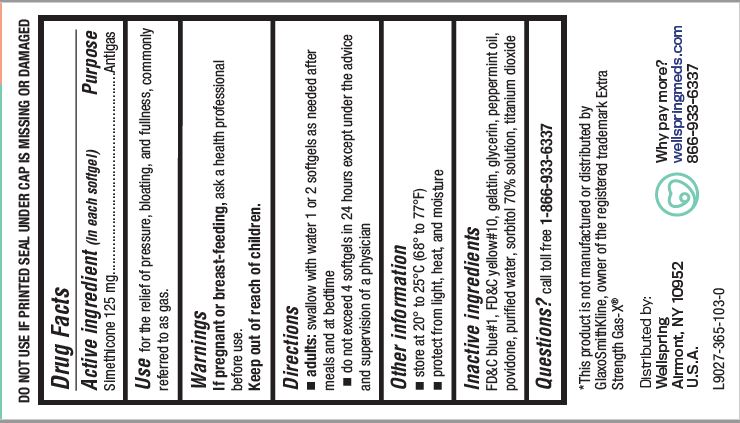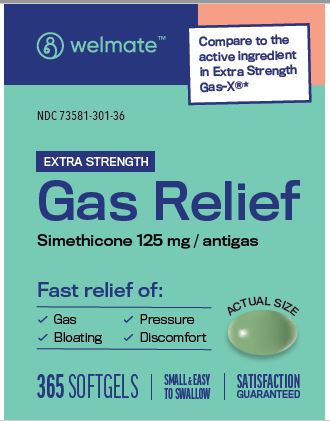 DRUG LABEL: GAS RELIEF
NDC: 73581-301 | Form: CAPSULE, LIQUID FILLED
Manufacturer: YYBA CORP
Category: otc | Type: HUMAN OTC DRUG LABEL
Date: 20240103

ACTIVE INGREDIENTS: DIMETHICONE 125 mg/1 1
INACTIVE INGREDIENTS: SORBITOL SOLUTION 70%; FD&C BLUE NO. 1; D&C YELLOW NO. 10; GELATIN; TITANIUM DIOXIDE; GLYCERIN; PEPPERMINT OIL; POVIDONE; WATER

YYBA (as PLD) - WELMATE GAS RELIEF - SIMETHICONE 125 MG (73581-301)

Active ingredient (in each softgel)

Simethicone 125 mg

Purpose

Antigas

Uses

for the relief of pressure, bloating, and fullness, commonly referred to as gas.

Warnings

If pregnant or breast-feeding, ask a health professional before use.

Keep out of reach of children.

Directions

■ adults: swallow with water 1 or 2 softgels as needed after meals and at bedtime

■ do not exceed 4 softgels in 24 hours except under the advice and supervision of a physician

Other information

■ store at 20° to 25°C (68° to 77°F)
■ protect from light, heat and moisture

Inactive ingredients

FD&C blue #1, FD&C yellow #10, gelatin, glycerin, peppermint oil, povidone, puriﬁed water, sorbitol 70% solution, titanium dioxide.

Questions?

call toll free 1-866-933-6337